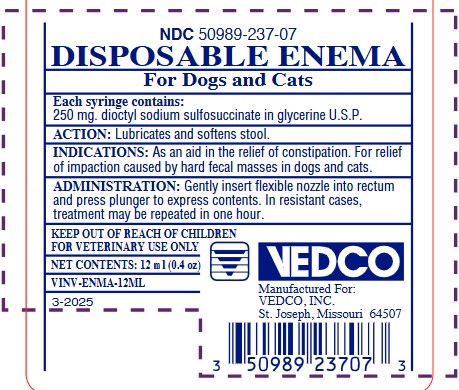 DRUG LABEL: DISPOSABLE ENEMA
NDC: 50989-237 | Form: ENEMA
Manufacturer: Vedco Incorporated
Category: animal | Type: OTC ANIMAL DRUG LABEL
Date: 20251229

ACTIVE INGREDIENTS: DOCUSATE SODIUM 250 mg/12 mL

DESCRIPTION

Disposable Enema for Dogs and Cats

Each syringe contains:

250 mg. dioctyl sodium sulfosuccinate in glycerine U.S.P.

ACTION:

Lubricates and softens stool.

INDICATIONS:

As an aid in the relief of constipation.

For relief of impaction caused by hard fecal masses in dogs and cats.

ADMINISTRATION:

Gently insert flexible nozzle into rectum and press plunger to express contents. In resistant cases, treatment may be repeated in one hour.

WARNINGS:

KEEP OUT OF REACH OF CHILDREN

FOR VETERINARY USE ONLY

NET CONTENTS:

12 mL

PRINCIPAL DISPLAY PANEL:

NDC 50989-237-07

DISPOSABLE ENEMA

For Dogs and Cats

NET CONTENTS: 12 mL

VEDCO

Manufactured For:

VEDCO, INC.

St. Joseph, Missouri 64507